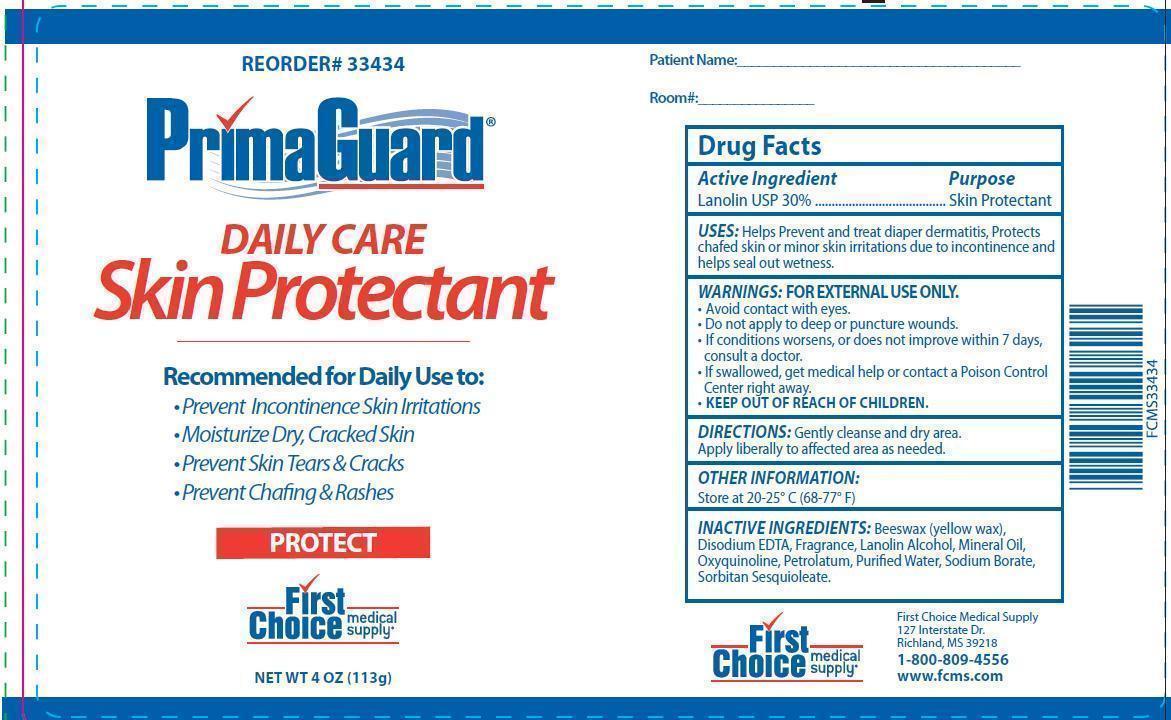 DRUG LABEL: PrimaGuard
NDC: 75904-3343 | Form: OINTMENT
Manufacturer: First Choice Medical Supply
Category: otc | Type: HUMAN OTC DRUG LABEL
Date: 20130321

ACTIVE INGREDIENTS: LANOLIN 300 mg/1 g
INACTIVE INGREDIENTS: YELLOW WAX; EDETATE DISODIUM; LANOLIN ALCOHOLS; MINERAL OIL; OXYQUINOLINE; PETROLATUM; WATER; SODIUM BORATE; SORBITAN SESQUIOLEATE

PrimaGuard Daily Care Skin Protectant Drug Facts

Active Ingredient

Lanolin USP 30%

Purpose

Skin Protectant

Uses

- Helps prevent and treat skin irritations.
- Protects chafed skin or minor skin irritations due to incontinence and helps seal out wetness.

Warnings: FOR EXTERNAL USE ONLY

- Avoid contact with eyes.
- Do not apply to deep or puncture wounds.
- If condition worsens, or does not improve within 7 days, consult a doctor.
- If swallowed, get medical help or contact a Poison Control Center right away.

- KEEP OUT OF REACH OF CHILDREN.

Directions

Gently cleanse and dry area. Apply liberally to affected area as needed.

Other Information

Store at 20-25°C (68-77°F)

Inactive ingredients:

Beeswax (yellow wax), Disodium EDTA, Fragrance, Lanolin Alcohol, Mineral Oil, Oxyquinoline, Petrolatum, Purified Water, Sodium Borate, Sorbitan Sesquioleate

Questions or comments?

Call 800-809-4556

or visit www.fcms

First Choice Medical Supply

127 Interstate Dr.

Richland, MS 39218

Images of representative container artwork

PrimaGuardProtectTubeLabel.jpg